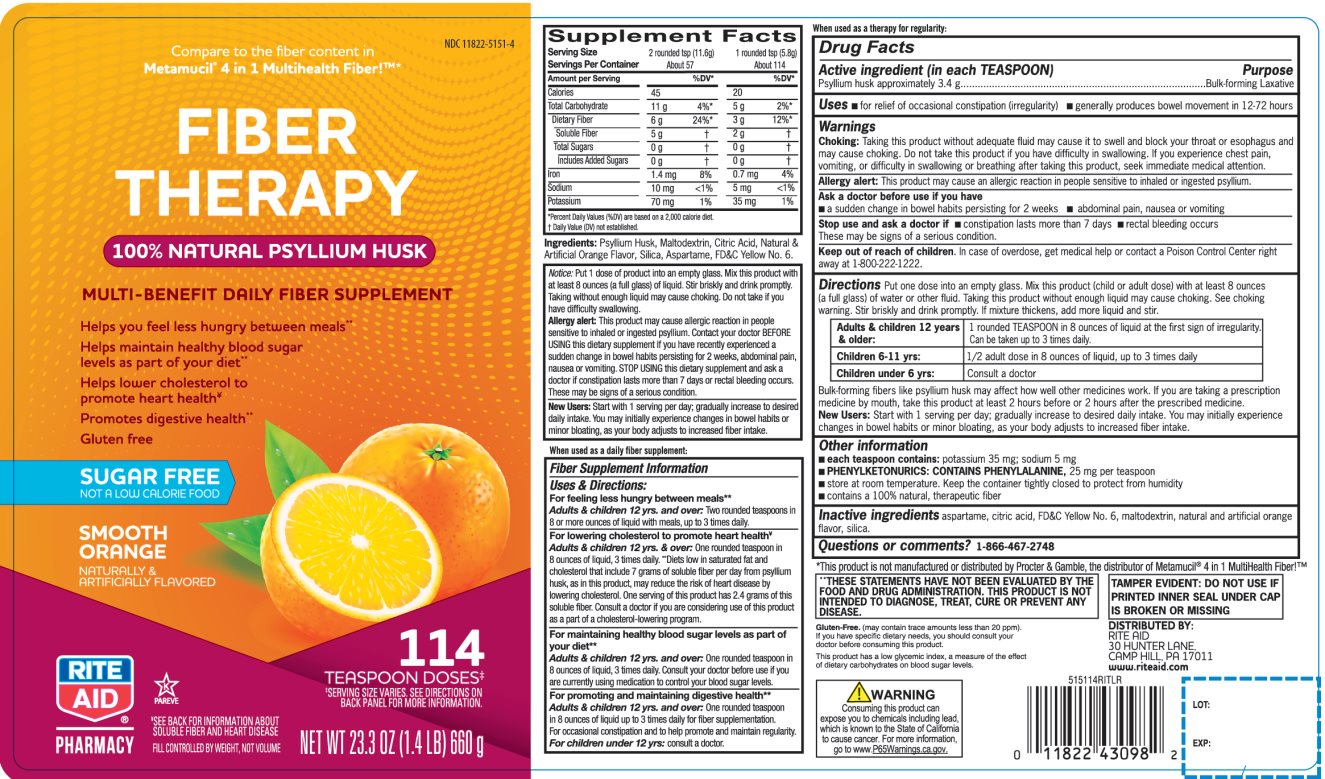 DRUG LABEL: Rite Aid Fiber Therapy
NDC: 11822-5151 | Form: POWDER, FOR SUSPENSION
Manufacturer: RITE AID CORPORATION
Category: otc | Type: HUMAN OTC DRUG LABEL
Date: 20211025

ACTIVE INGREDIENTS: PSYLLIUM HUSK 3.4 g/5.8 g
INACTIVE INGREDIENTS: ASPARTAME; ANHYDROUS CITRIC ACID; FD&C YELLOW NO. 6; MALTODEXTRIN; SILICON DIOXIDE

Quality Choice Natural Fiber Powder

Active ingredient (in each TEASPOON)

Psyllium husk approximately 3.4 g

Purpose

Fiber therapy for regularity

Uses

- for relief of occasional constipation (irregularity)

Warnings

Allergy alert: This product may cause allergic reaction in people sensitive to inhaled or ingested psyllium.

Choking: Taking this product without adequate fluid may cause it to swell and block your throat or esophagus and may cause choking. Do not take this product if you have difficulty in swallowing. If you experience chest pain, vomiting, or difficulty in swallowing or breathing after taking this product, seek immediate medical attention.

Ask a doctor before use if you have

- abdominal pain, nausea or vomiting
- a sudden change in bowel habits persisting for 2 weeks

Stop use and ask a doctor if

- Constipation lasts more than 7 days
- Rectal bleeding occurs

These may be signs of a serious condition.

Keep Out of Reach of Children

In case of overdose, get medical help or contact a Poison Control Center right away at 1-800-222-1222.

Directions:

Put one dose into an empty glass. Mix this product (child or adult dose) with at least 8 ounces (a full glass) of water or other fluid. Taking this product without enough liquid may cause choking. See choking warning. Stir briskly and drink promptly. If mixture thickness, add more liquid and stir.

Adults 12 years & older: | 1 rounded TEASPOON in 8 ounces of liquid at the signs of irregularity. Can be taken up to 3 times daily. Generally produces effect in 12-72 hours.
Children 6-11 yrs: | ½ adult dose in 8 ounces of liquid, up to 3 times daily
Under 6 yrs: | Consult a doctor

Bulk-forming fibers like psyllium husk may affect how well other medicines work. If you are taking a prescription medicine by mouth, take this product at least 2 hours before or 2 hours after the prescribed medicine.

New Users: Start with 1 serving per day; gradually increase to desired daily intake. You may initially experience changes in bowel habits or minor bloating, as your body adjusts to increased fiber intake.

Other information

- each teaspoon contains: potassium 35 mg and sodium 5 mg
- PHENYLKETONURICS: CONTAINS PHENYLALANINE, 25 mg per teaspoon
- Store at room temperature. Keep the container tightly closed to protect from humidity
- Contains a 100% natural, therapeutic fiber

Inactive ingredients

aspartame, citric acid, FD&C Yellow No. 6, maltodextrin, natural and artificial orange flavor, silica.

Questions or comments?

1-866-467-2748

Principal Display Panel

RITE AID PHARMACY®

NDC# 11822-5151-4

Compare to the fiber content in Metamucil® 4 in 1 MultiHealth Fiber!™*

FIBER THERAPY

100% NATURAL PSYLLIUM HUSK

MULTI-BENEFIT DAILY FIBER SUPPLEMENT

Helps you feel less hungry between meals**

Helps Maintain Healthy Blood Sugar Levels as Part of Your Diet**

Helps Lower Cholesterol to Promote Heart Health‡

Promotes Digestive Health**

Gluten Free

SUGAR FREE

NOT A LOW CALORIE FOOD

SMOOTH ORANGE

NATURALLY & ARTIFICIALLY FLAVORED

**SEE BACK FOR INFORMATION ABOUT SOLUBLE FIBER AND HEART DISEASE.

114 TEASPOON DOSES

SERVING SIZE VARIES. SEE DIRECTIONS ON BACK PANEL FOR MORE INFORMATION

K PAREVE

NET WT. 23.3 OZ (1.4 LB) 660g

FILL CONTROLLED BY WEIGHT, NOT VOLUME

†THESE STATEMENTS HAVE NOT BEEN EVALUATED BY THE FOOD AND DRUG ADMINISTRATION. THIS PRODUCT IS NOT INTENDED TO DIAGNOSE, TREAT, CURE OR PREVENT ANY DISEASE.

TAMPER EVIDENT: DO NOT USE IF PRINTED INNER SEAL UNDER CAP IS BROKEN OR MISSING

*This product is not manufactured or distributed by Procter & Gamble, the distributor, the distributor of Metamucil® 4 in 1 MultiHealth Fiber!™*

DISTRIBUTED BY:

RITE AID

30 HUNTER LANE,

CAMP HILL, PA 17011

www.riteaid.com